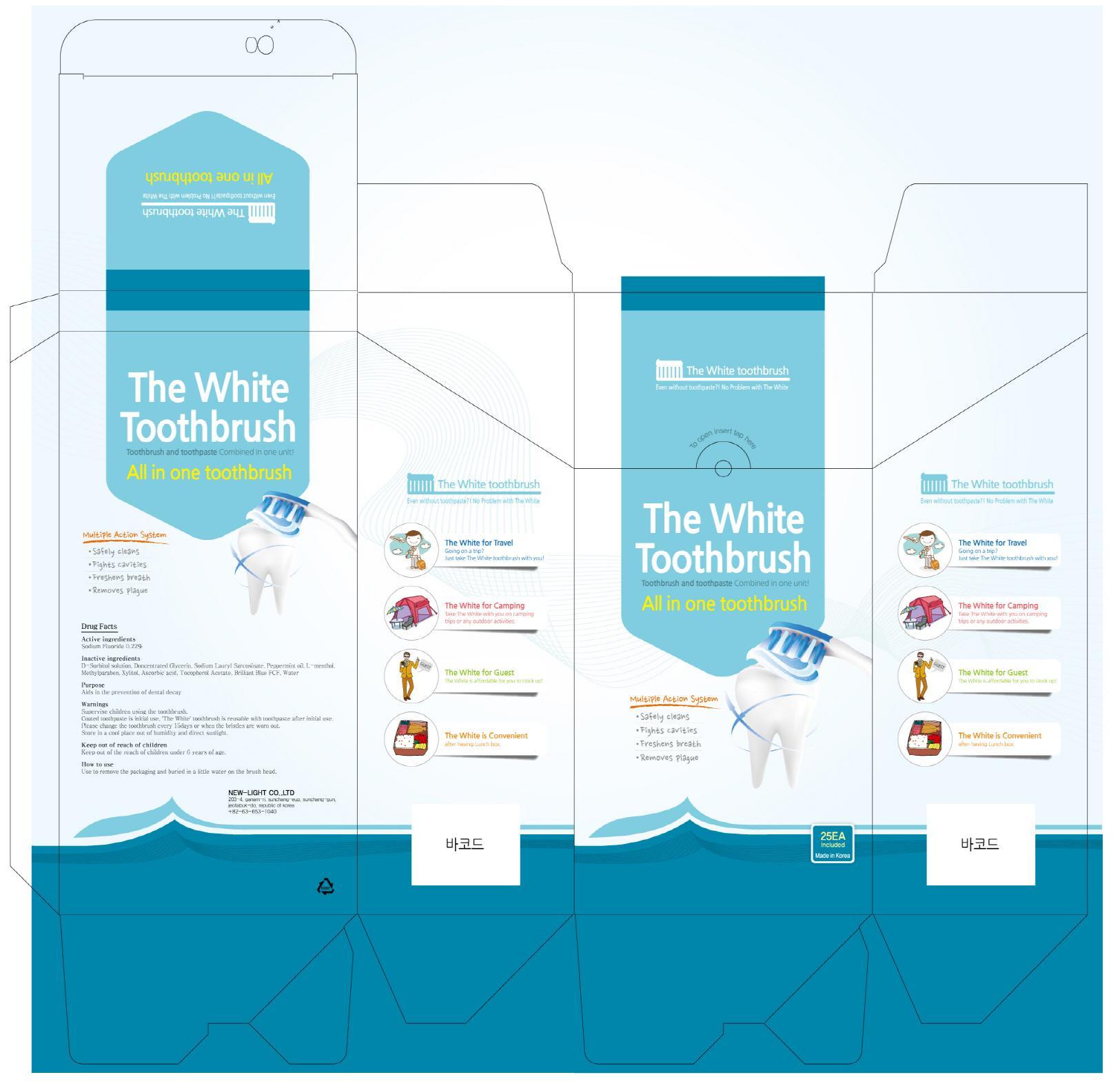 DRUG LABEL: The White Toothbrush
NDC: 69370-020 | Form: GEL, DENTIFRICE
Manufacturer: New-Light Co., Ltd
Category: otc | Type: HUMAN OTC DRUG LABEL
Date: 20150224

ACTIVE INGREDIENTS: Sodium Fluoride 0.0002 g/25 1
INACTIVE INGREDIENTS: Peppermint oil; Xylitol

ACTIVE INGREDIENT

Active ingredient: Sodium Fluoride 0.22%

INACTIVE INGREDIENT

Inactive ingredients: D-Sorbitol solution, Doncentrated Glycerin, Sodium Lauryl Sarcosinate, Peppermint oil, L-menthol, Methylparaben, Xylitol, Ascorbic acid, Tocopherol Acetate, Brilliant Blue FCF, Water

PURPOSE

Purpose: Aids in the prevention of dental decay

WARNINGS

Warnings: Supervise children using the toothbrush. Coated toothpaste is initial use, 'The Blue' toothbrush is reusable with toothpaste after initial use. Please change the toothbrush every 15days or when the bristles are worn out. Store in a cool place out of humidity and direct sunlight.

Keep out of reach of children: Keep out of the reach of children under 6 years of age.

How to use: Use to remove the packaging and buried in a little water on the brush head.

How to use: Use to remove the packaging and buried in a little water on the brush head.

PACKAGE LABEL.PRINCIPAL DISPLAY PANEL

Image of carton